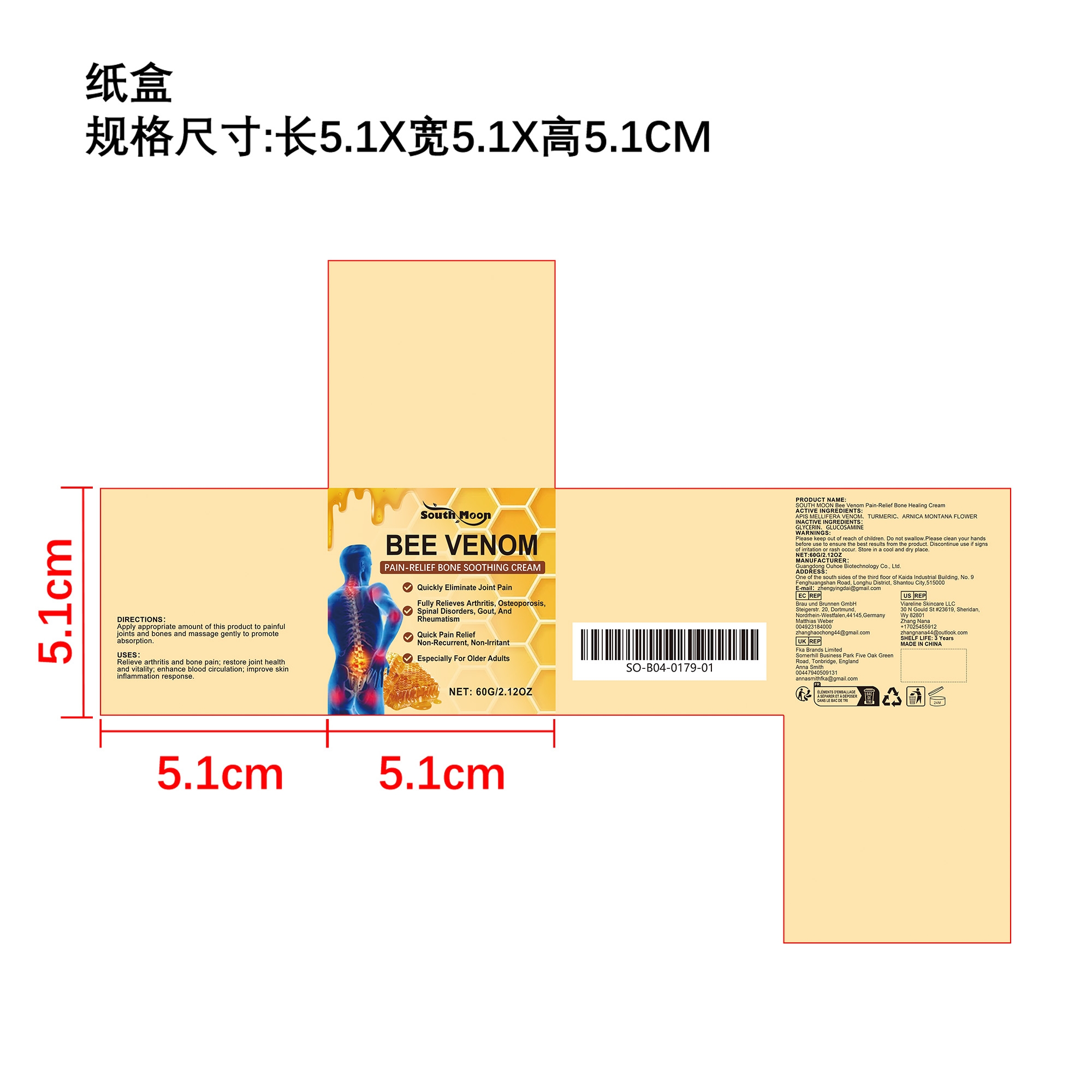 DRUG LABEL: SOUTH MOON Bee Venom Pain-Relief Bone Healing Cream
NDC: 84744-058 | Form: CREAM
Manufacturer: Guangdong Ouhoe Biotechnology Co., Ltd.
Category: otc | Type: HUMAN OTC DRUG LABEL
Date: 20241022

ACTIVE INGREDIENTS: APIS MELLIFERA VENOM 10 g/60 g; TURMERIC 14 g/60 g; ARNICA MONTANA FLOWER 6 g/60 g
INACTIVE INGREDIENTS: GLUCOSAMINE 10 g/60 g; GLYCERIN 20 g/60 g

Active Ingredient(s)

APIS MELLIFERA VENOM、TURMERIC、ARNICA MONTANA FLOWER

Purpose

Relieve arthritis and bone pain; restore joint health and vitality; enhance blood circulation; improve skin inflammation response.

Use

Apply appropriate amount of this product to painful joints and bones and massage gently to promote absorption.

Warnings

Please keep out of reach of children.Do not swallow.Please clean your hands before use to ensure the best results from the product.Discontinue use if signs of irritation or rash occur.Store in a cool and dry place.

Do not use

Discontinue use if signs of irritation or rash occur.

Stop Use

Discontinue use if signs of irritation or rash occur.

KEEP OUT OF REACH OF CHILDREN

Please keep out of reach of children. Do not swallow.

STORAGE AND HANDLING

Store in a cool and dry place.

INACTIVE INGREDIENT

GLYCERIN、GLUCOSAMINE